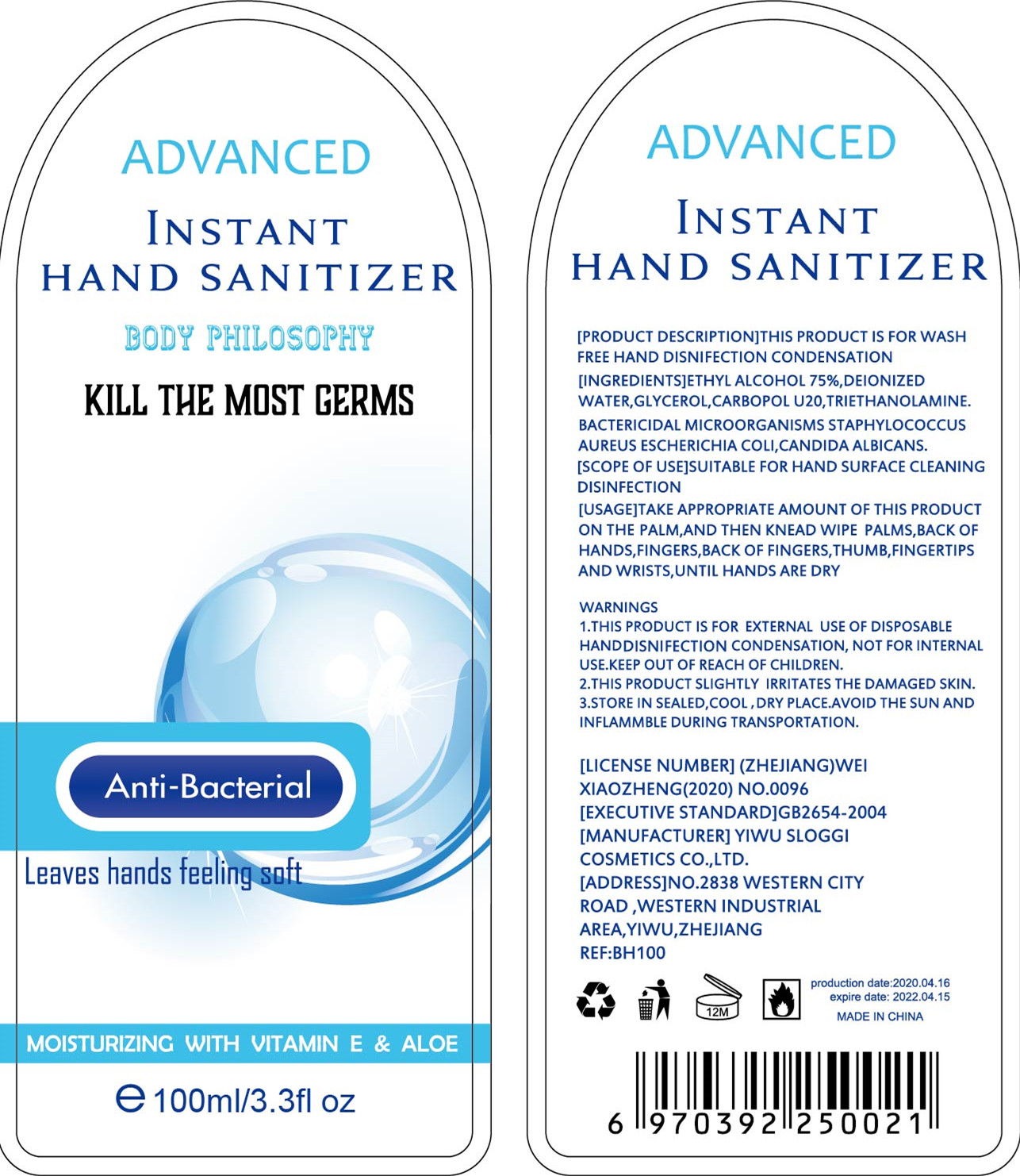 DRUG LABEL: Hand sanitizer
NDC: 54225-001 | Form: LIQUID
Manufacturer: YIWU SLOGGI COSMETICS CO.,LTD
Category: otc | Type: HUMAN OTC DRUG LABEL
Date: 20200410

ACTIVE INGREDIENTS: ALCOHOL 75 mL/100 mL
INACTIVE INGREDIENTS: CARBOMER HOMOPOLYMER, UNSPECIFIED TYPE; WATER; TROLAMINE

DOSAGE AND ADMINISTRATION

STORE IN SEALED,COOL。DRY PLACE.AVOID THE SUN AND INFLAMMBLE DURING TRANSPORTATION.

INACTIVE INGREDIENT

AQUA

TRIETHANOLAMINE

CARBOMER

INDICATIONS AND USAGE

TAKE APPROPRIATE AMOUNT OF THIS PRODUCT ON THE PALM,AND THEN KNEAD WIPE PALMS,BACK OF

HANDS,FINGERS,BACK OF FINGERS,THUMB,FINGERTIPS AND WRISTS,UNTIL HANDS ARE DRY

ACTIVE INGREDIENT

ALCOHOL

keep out of children

PURPOSE

Disinfection
Sterilization
No Rinseing

WARNINGS

1.THIS PRODUCT IS FOR EXTERNAL USE OF DISPOSABLE HANDDISNIFECTION CONDENSATION, NOT FOR INTERNAL
USE.KEEP OUT OF REACH OF CHILDREN.
2.THIS PRODUCT SLIGHTLY IRRITATES THE DAMAGED SKIN.
3.STORE IN SEALED,COOL。DRY PLACE.AVOID THE SUN AND INFLAMMBLE DURING TRANSPORTATION.